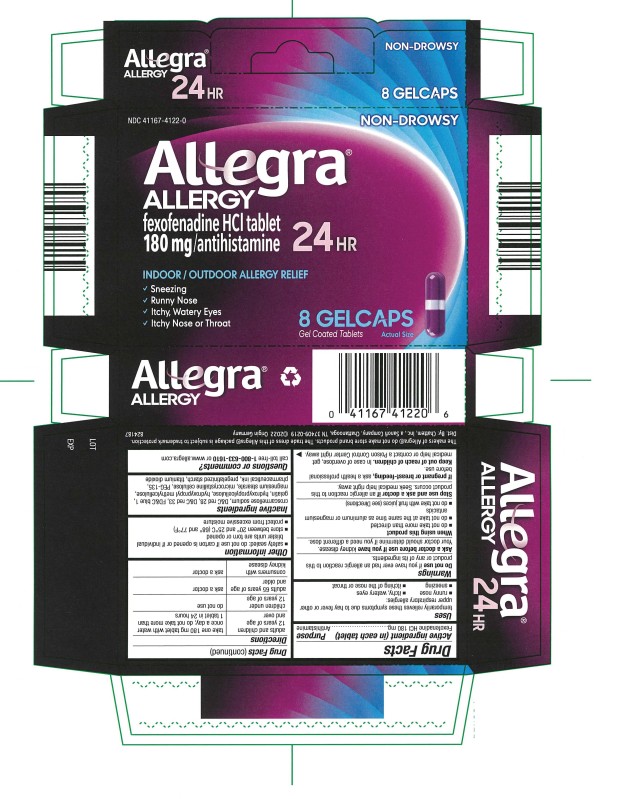 DRUG LABEL: Allegra Allergy
NDC: 41167-4122 | Form: TABLET, COATED
Manufacturer: Chattem, Inc.
Category: otc | Type: HUMAN OTC DRUG LABEL
Date: 20250219

ACTIVE INGREDIENTS: FEXOFENADINE HYDROCHLORIDE 180 mg/1 1
INACTIVE INGREDIENTS: CROSCARMELLOSE SODIUM; D&C RED NO. 28; D&C RED NO. 33; FD&C BLUE NO. 1; GELATIN; HYDROXYPROPYL CELLULOSE (1600000 WAMW); HYPROMELLOSES; MAGNESIUM STEARATE; CELLULOSE, MICROCRYSTALLINE; POLYETHYLENE GLYCOL 6000; STARCH, CORN; TITANIUM DIOXIDE

Allegra Allergy

Allegra Allergy® Gelcaps – 24 HOUR

Drug Facts

Active ingredient

(in each tablet)

Fexofenadine HCI 180 mg

Purpose

Antihistamine

Uses

temporarily relieves these symptoms due to hay fever or other upper respiratory allergies:

- runny nose
- sneezing
- itchy, water eyes
- itching of the nose or throat

Warnings

Do not use

if you have ever had an allergic reaction to this product or any of its ingredients.

Ask a doctor before use if you have

kidney disease. Your doctor should determine if you need a different dose.

When using this product

- do not take more than directed
- do not take at the same time as aluminum or magnesium antacids
- do not take with fruit juices (see Directions)

Stop use and ask a doctor if

an allergic reaction to this product occurs. Seek medical help right away.

If pregnant or breast-feeding,

ask a health professional before use.

Keep out of reach of children.

In case of overdose, get medical help or contact a Poison Control Center right away.

Directions

adults and children 12 years of age and over | take one 180 mg tablet with water once a day; do not take more than 1 tablet in 24 hours
children under 12 years of age | do not use
adults 65 years of age and older | ask a doctor
consumers with kidney disease | ask a doctor

Other information

- safety sealed: do not use if carton is opened or if individual blister units are torn or opened
- store between 20º and 25ºC (68º and 77ºF)
- protect from excessive moisture

Inactive ingredients

croscarmellose sodium, D&C red 28, D&C red 33, FD&C blue 1, gelatin, hydroxypropylcellulose, hydroxypropyl methylcellulose, magnesium stearate, microcrystalline cellulose, PEG-135, pharmaceutical ink, pregelatinized starch, titanium dioxide

Questions or comments?

call toll-free 1-800-633-1610 or www.allegra.com

The makers of Allegra® do not make store brand products. The trade dress of this Allegra® package is subject to trademark protection.
Dist. By: Chattem, Inc., a Sanofi Company, Chattanooga, TN 37409-0219 ©2014

PRINCIPAL DISPLAY PANEL

NDC 41167-4122-0
Allegra®
ALLERGY
fexofenadine HCI tablet
180 mg/antihistamine
24 HR
8 GELCAPS